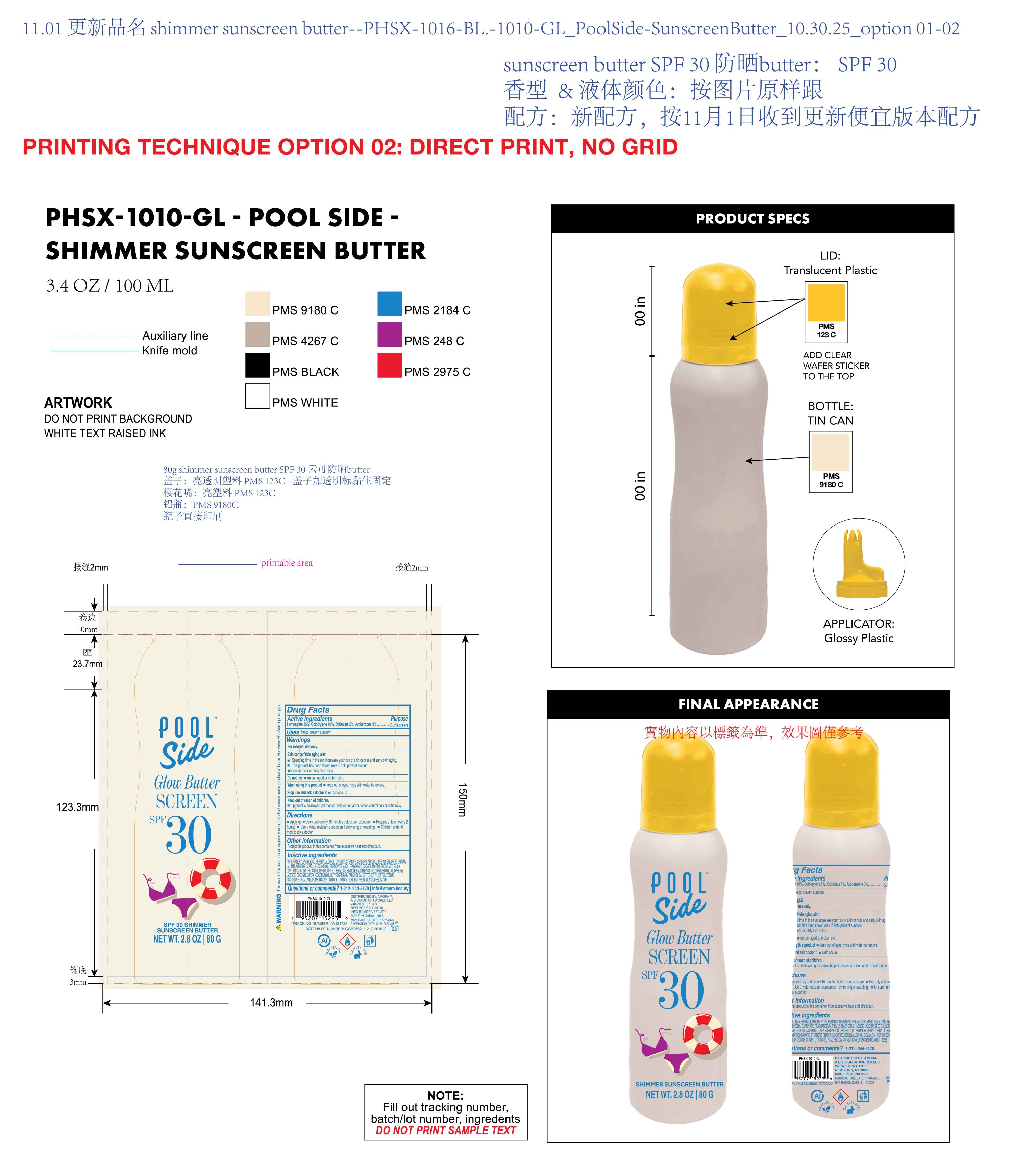 DRUG LABEL: Poolside Glow Butter Screen  SPF 30 Shimmer sunscreen Butter
NDC: 85161-166 | Form: OIL
Manufacturer: Longway Technology(Guangzhou)Co.,Ltd.
Category: otc | Type: HUMAN OTC DRUG LABEL
Date: 20251204

ACTIVE INGREDIENTS: AVOBENZONE 0.03 g/1 g; HOMOSALATE 0.15 g/1 g; OCTISALATE 0.05 g/1 g; OCTOCRYLENE 0.1 g/1 g
INACTIVE INGREDIENTS: BEHENYL ALCOHOL; PEG-100 STEARATE; CI 77891; ETHYLHEXYLGLYCERIN; CI 77491; CALCIUM ALUMINUM BOROSILICATE; 1,2-HEXANEDIOL; PHENOXYETHANOL; XANTHAN GUM; ALPHA-TOCOPHEROL ACETATE; GLYCERYL STEARATE; POTASSIUM CETYL PHOSPHATE; CETEARYL ALCOHOL; SILICA; EDETATE DISODIUM; PROPYLENE GLYCOL; FRAGRANCE 13576; METHICONE (20 CST); TREHALOSE; MAGNESIUM POTASSIUM ALUMINOSILICATE FLUORIDE; COCOS NUCIFERA (COCONUT) OIL; BUTYROSPERMUM PARKII (SHEA) BUTTER; WATER; SIMMONDSIA CHINENSIS (JOJOBA) SEED OIL; ALLANTOIN; TIN OXIDE

ACTIVE INGREDIENT

Homosalate 15%, Octocrylene 10%, Octisalate 5% , Avobenzone 3%

PURPOSE

Sunscreen

DOSAGE AND ADMINISTRATION

Apply generously and evenly 15 minutes before sun exposure.

Reapply at least every 2hours.

Use a water resistant sunscreen if swimming or sweating.m

Children under 6 month: ask a doctor.

QUESTIONS

1-212-244-5170 I info@amora.beauty

OTHER SAFETY INFORMATION

Protect the product in this container from excessive heat and direct sun.

WARNINGS

For extetnal use only.
Skin cancer/skin aging alert
Spending time in the sun increases your risk of skin cancer and early skin aging.

This product has been shown only to help prevent sunburn,not skin cancer or early skin aging.

Do not use on damaged or broken skin.

When using this product keep out of eyes. rinse with water to remove.

Stop use and ask a doctor if rash occurs

Keep out of reach of children.

lf product is swallowed get medical help or contact a poison control center right away.

KEEP OUT OF REACH OF CHILDREN

If product is swallowed get medical help or contact a poison control center right away.

INDICATIONS AND USAGE

Helps prevent sunburn.

INACTIVE INGREDIENT

WATER，PROPYLENE GLYCOL，BEHENYL ALCOHOL，GLYCERYL STEARATE，CETEARYL ALCOHOL，PEG-100 STEARATE，CALCIUM ALUMINUM BOROSILICATE，1,2-HEXANEDIOL，PHENOXYETHANOL，FRAGRANCE，POTASSIUM CETYL PHOSPHATE，SILICA，XANTHAN GUM，SYNTHETIC FLUORPHLOGOPITE，TREHALOSE，SIMMONDSIA CHINENSIS (JOJOBA) SEED OIL，TOCOPHERYL ACETATE，COCOS NUCIFERA (COCONUT) OIL，BUTYROSPERMUM PARKII (SHEA) BUTTER，ETHYLHEXYLGLYCERIN，DISODIUM EDTA，ALLANTOIN，METHICONE，TIN OXIDE，TITANIUM DIOXIDE(CI 77891)，IRON OXIDES(CI 77491)